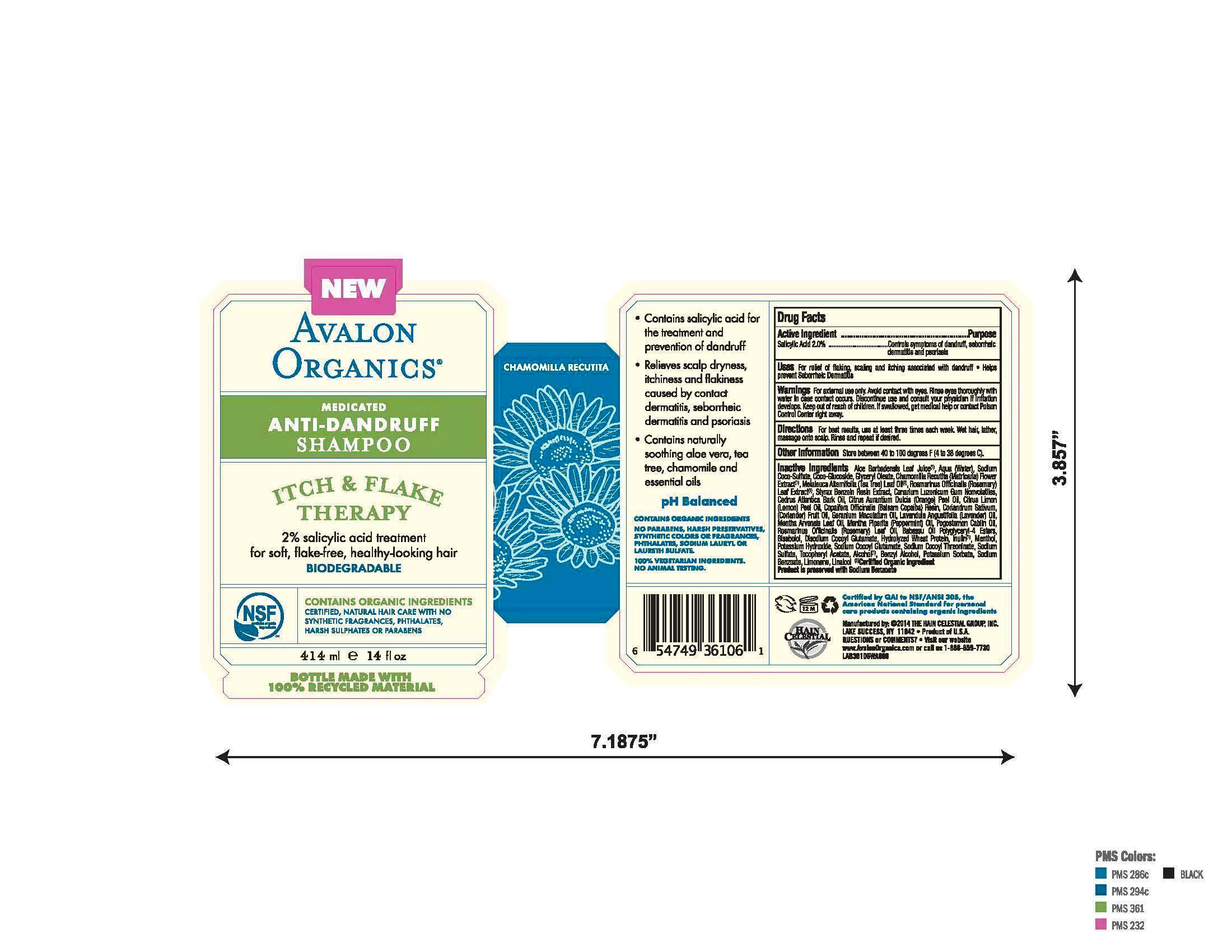 DRUG LABEL: Anti Dandruff
NDC: 61995-1106 | Form: SHAMPOO
Manufacturer: The Hain Celestial Group, Inc.
Category: otc | Type: HUMAN OTC DRUG LABEL
Date: 20140128

ACTIVE INGREDIENTS: SALICYLIC ACID 2.0 g/414 g
INACTIVE INGREDIENTS: ALOE VERA LEAF; WATER; SODIUM COCO-SULFATE; COCO GLUCOSIDE; GLYCERYL OLEATE; CHAMOMILE; MELALEUCA ALTERNIFOLIA LEAF; ROSMARINUS OFFICINALIS FLOWER; STYRAX BENZOIN RESIN; CANARIUM LUZONICUM WHOLE; CEDRUS ATLANTICA BARK OIL; ORANGE OIL; LEMON OIL; COPAIFERA OFFICINALIS RESIN; CORIANDER OIL; GERANIUM MACULATUM WHOLE; LAVENDER OIL; MENTHA ARVENSIS LEAF OIL; MENTHA PIPERITA; POGOSTEMON CABLIN WHOLE; ROSEMARY OIL; .ALPHA.-BISABOLOL, (+)-; DISODIUM COCOYL GLUTAMATE; HYDROLYZED WHEAT PROTEIN (ENZYMATIC, 3000 MW); INULIN; MENTHOL; POTASSIUM HYDROXIDE; SODIUM COCOYL GLUTAMATE; SODIUM SULFATE; .ALPHA.-TOCOPHEROL ACETATE; ALCOHOL; BENZYL ALCOHOL; POTASSIUM SORBATE; SODIUM BENZOATE

WARNINGS

For external use only. Avoid contact with eyes. Rinse eyes throughly with water in case contact ossurs. Discontinue to use and contact your physician if irritation develops.

Drug Facts

Salicylic Acid 2.0%

PURPOSE

Controls symptoms of dandruff, seboric dermatitis and psoriasis

Keep out of reach of children. If swallowed, get medical help or contact Poison Control Center right away.

INDICATIONS AND USAGE

For relief of flaking, scaling and itching associated with dandruff. Helps prevent Seborrheic Dermatitis

DOSAGE AND ADMINISTRATION

For the best results use at least three times each week. Wet hair, lather, massage onto scalp. Rinse and repeat if desired.

INACTIVE INGREDIENT

Aloe Barbadensis Leaf Juice (1),Aqua (Water), Sodium Coco-Sulfate, Cococ-Glucoside, Glyceryl Oleate, Chamomilla Recuitita (Matricaria) Flower Extract (1), Malaleuca Alternifolia (Tea Tree) Leaf Oil (1), Rosmarinus Officinalis (Rosemary) extract, Styrax Benzoin Resin Extract (1), Canarium Luzonicum Gum Nonvolatiles, Cedrus Atlantica Bark Oil, Citrus Aurantium Dulcis (Orange Peel Oil, Citrus Limon (Lemon) Peel Oil,